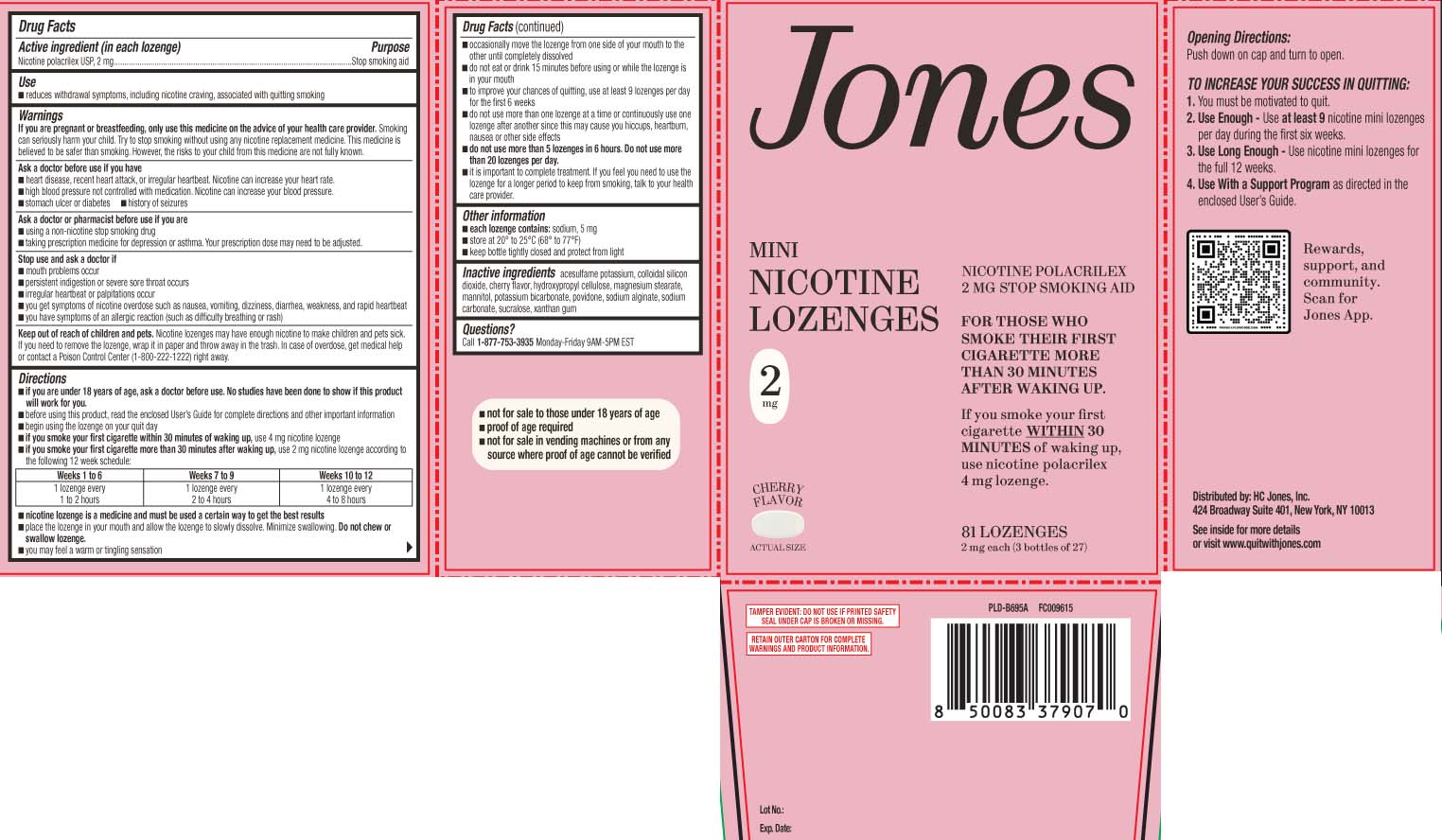 DRUG LABEL: Nicotine
NDC: 83253-978 | Form: LOZENGE
Manufacturer: HC Jones, Inc.
Category: otc | Type: HUMAN OTC DRUG LABEL
Date: 20260217

ACTIVE INGREDIENTS: NICOTINE 2 mg/1 1
INACTIVE INGREDIENTS: ACESULFAME POTASSIUM; SILICON DIOXIDE; HYDROXYPROPYL CELLULOSE, UNSPECIFIED; MAGNESIUM STEARATE; MANNITOL; POTASSIUM BICARBONATE; POVIDONE; SODIUM ALGINATE; SODIUM CARBONATE; SUCRALOSE; XANTHAN GUM

Drug Facts

Active ingredient (in each lozenge)

Nicotine polacrilex USP, 2 mg

Purpose

Stop smoking aid

Use

- reduces withdrawal symptoms, including nicotine craving, associated with quitting smoking

Warnings

If you are pregnant or breast-feeding,

only use this medicine on the advice of your health care provider. Smoking can seriously harm your child. Try to stop smoking without using any nicotine replacement medicine. This medicine is believed to be safer than smoking. However, the risks to your child from this medicine are not fully known.

Ask a doctor before use if you have

- heart disease, recent heart attack, or irregular heartbeat. Nicotine can increase your heart rate.
- high blood pressure not controlled with medication. Nicotine can increase your blood pressure.
- stomach ulcer or diabetes
- history of seizures

Ask a doctor or pharmacist before use if you are

- using a non-nicotine stop smoking drug
- taking prescription medicine for depression or asthma. Your prescription dose may need to be adjusted.

Stop use and ask a doctor if

- mouth problems occur
- persistent indigestion or severe sore throat occurs
- irregular heartbeat or palpitations occur
- you get symptoms of nicotine overdose such as nausea, vomiting, dizziness, diarrhea, weakness and rapid heartbeat
- you have symptoms of an allergic reaction (such as difficulty breathing or rash)

Keep out of reach of children and pets.

Nicotine lozenges may have enough nicotine to make children and pets sick. If you need to remove the lozenge, wrap it in paper and throw away in the trash. In case of overdose, get medical help or contact a Poison Control Center (1-800-222-1222) right away.

Directions

- if you are under 18 years of age, ask a doctor before use. No studies have been done to show if this product will work for you.
- before using this product, read the enclosed User’s Guide for complete directions and other important information
- begin using the lozenge on your quit day
- if you smoke your first cigarette within 30 minutes of waking up, use 4 mg nicotine lozenge
- if you smoke your first cigarette more than 30 minutes after waking up, use 2 mg nicotine lozenge according to the following 12 week schedule:

Weeks 1 to 6 | Weeks 7 to 9 | Weeks 10 to 12
1 lozenge every 1 to 2 hours | 1 lozenge every 2 to 4 hours | 1 lozenge every 4 to 8 hours

- nicotine lozenge is a medicine and must be used a certain way to get the best results
- place the lozenge in your mouth and allow the lozenge to slowly dissolve (about 20 to 30 minutes). Minimize swallowing. Do not chew or swallow lozenge.
- you may feel a warm or tingling sensation
- occasionally move the lozenge from one side of your mouth to the other until completely dissolved (about 20 to 30 minutes)
- do not eat or drink 15 minutes before using or while the lozenge is in your mouth
- to improve your chances of quitting, use at least 9 lozenges per day for the first 6 weeks
- do not use more than one lozenge at a time or continuously use one lozenge after another since this may cause you hiccups, heartburn, nausea or other side effects
- do not use more than 5 lozenges in 6 hours. Do not use more than 20 lozenges per day.
- It is important to complete treatment. If you feel you need to use the lozenge for a longer period to keep from smoking, talk to your health care provider.

Other information

- each lozenge contains: sodium 5 mg
- store at 20º to 25ºC (68º to 77ºF)
- keep bottle tightly closed and protect from light

Inactive ingredients

acesulfame potassium, colloidal silicon dioxide, cherry flavor, hydroxypropyl cellulose, magnesium stearate, mannitol, potassium bicarbonate, povidone, sodium alginate, sodium carbonate, sucralose,xanthan gum

Questions or comments?

Call1-877-753-3935 Monday-Friday 9AM-5PM EST

Principal Display Panel

MINI

NICOTINE LOZENGE

NICOTINE POLACRILEX 2 mg

STOP SMOKING AID

FOR THOSE WHO SMOKE THEIR FIRST CIGARETTE MORE THAN 30 MINUTES AFTER WAKING UP.

If you smoke your first cigarette WITHIN 30 MINUTES of waking up, use Nicotine Polacrilex 4 mg lozenge.

Cherry Flavor

LOZENGES

TO INCREASE YOUR SUCCESS IN QUITTING:

1. You must be motivated to quit.

2. Use Enough - Use at least 9 Nicotine Polacrilex lozenges per day during the first six weeks.

3. Use Long Enough - Use Nicotine Polacrilex lozenges for the full 12 weeks.

4. Use With a Support Program as directed in the enclosed User's Guide.

- not for sale to those under 18 years of age
- proof of age required
- not for sale in vending machines or from any source where proof of age cannot be verified

TAMPER EVIDENT: DO NOT USE IF PRINTED SAFETY SEAL UNDER CAP IS BROKEN OR MISSING.

RETAIN OUTER CARTON FOR FULL PRODUCT USES, DIRECTIONS AND WARNINGS.

Distributed by: HC Jones, Inc.

424 Broadway Suite 401, New York, NY 10013

Package Label

JONES Mini Nicotine Lozenge Cherry Flavor